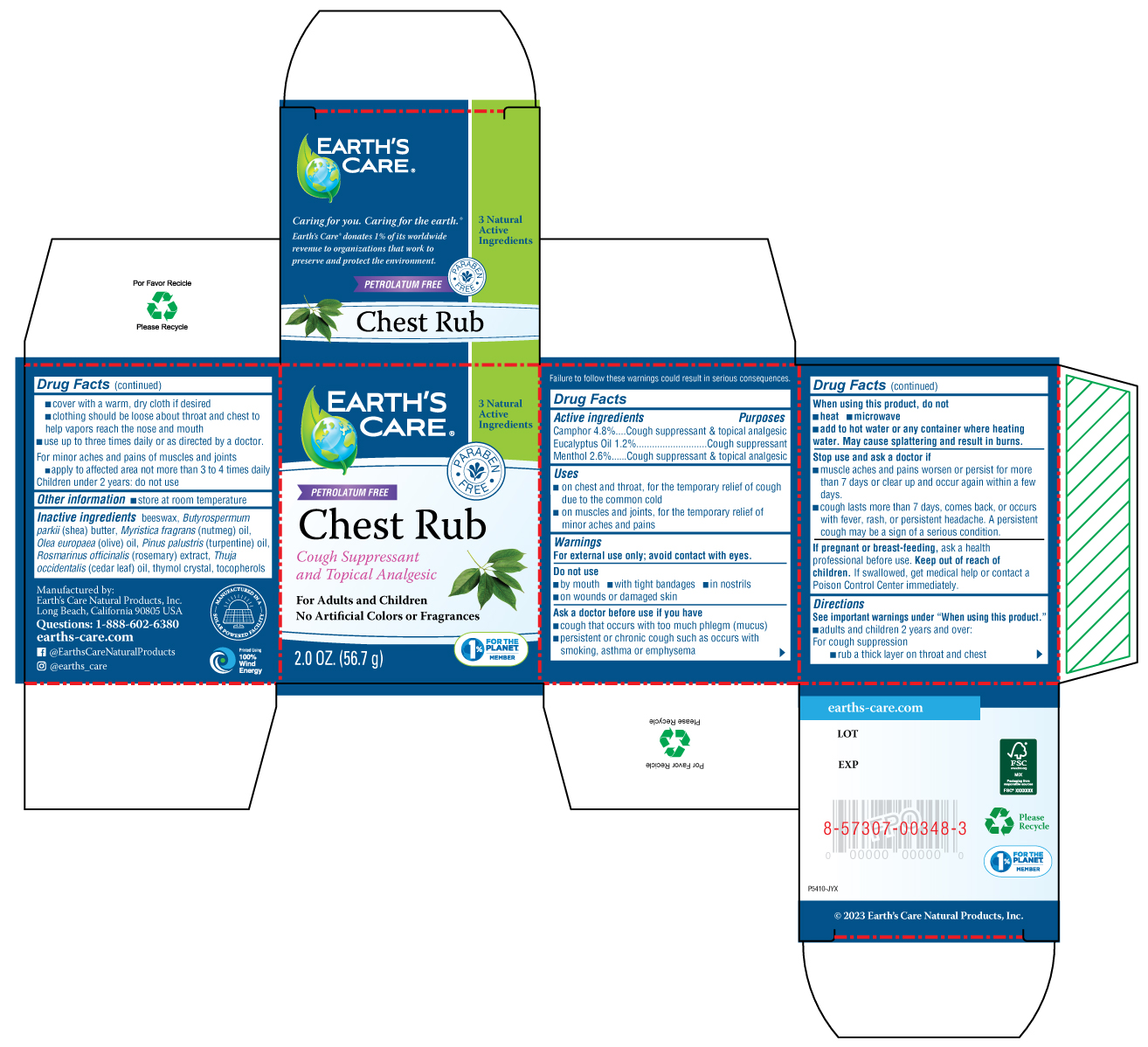 DRUG LABEL: Earths Care Chest Rub
NDC: 24286-1581 | Form: OINTMENT
Manufacturer: DLC Laboratories, Inc
Category: otc | Type: HUMAN OTC DRUG LABEL
Date: 20260107

ACTIVE INGREDIENTS: CAMPHOR (NATURAL) 4.8 g/100 g; MENTHOL 2.6 g/100 g; EUCALYPTUS OIL 1.2 g/100 g
INACTIVE INGREDIENTS: NUTMEG OIL; TOCOPHEROL; WHITE WAX; THYMOL; OLIVE OIL; TURPENTINE OIL; ROSEMARY; SHEA BUTTER; CEDAR LEAF OIL

Earths Care® Chest Rub

Active Ingredients

Camphor 4.8%

Eucalyptus Oil 1.2%

Menthol 2.6%

Purposes

Cough Suppressant & topical analgesic

Cough suppressant

Cough suppressant & topical analgesic

Uses

on chest and throat, for the temporary relief of cough due to the common cold

on muscles and joint, for the temporary relief of minor aches and pains

Warnings

For external use only; avoid contact with eyes

Do not Use

- by mouth
- with tight bandages
- in nostrils
- on wounds or damaged skin

Ask a doctor before use if you have

- cough that occurs with too much phlegm (mucus)
- persistent or chronic cough such as occurs with smoking, asthma, or emphysema

When using this product, do not

- heat
- microwave
- add to hot water or any container where heating water. May cause splattering and result in burns

Stop use and ask a doctor if

- muscle aches and pains worsen or persist for more than 7 days or clear up and occur again within a few days.
- cough lasts more than 7 days, comes back, or occurs with fever, rash, or persistent headache. A persistent cough may be a sign of a serious condition.

If pregnant or brease-feeding

ask a health professional before use.

Keep out of reach of children

If swallowed, get medical help or contact a Poison Control Center immediately.

Directions

See important warnings under "When using this product"

- adult and children 2 years and over:

For cough suppression

- rub a thick layer on throat and chest
- cover with a warm, dry cloth if desired
- clothing should be loose about throat and chest to help vapors reach the nose and mouth
- use up to three times daily or as directed by a doctor.

For minor aches and pains of muscles and joints

- apply to affected area not more than 3 to 4 times daily

Children under 2 years: do not use

Other information

- store at room temperature

Inactive ingredients

beeswax, Butyrospermum parkii (shea) butter, Myristica fragrans (nutmeg) oil, Olea europaea (olive) oil, Pinus palustris (turpentine) oil, Rosmarinus officinalis (rosemary) extract, Thuja occidentalis (cedar leaf) oil, thymol crystal, tocopherols

Questions

1-888-602-6380

earths-care.com

facebook @EarthsCareNaturalProducts

instagram @earths_care

Manufactured by

Earth's Care Natural Products, Inc.

Long Beach, California 90805 USA

PACKAGE LABEL

EARTH'S CARE®

3 Natural Active Ingredients

PARABEN FREE

PETROLATUM FREE

Chest Rub

Cough Suppressant

and Topical Analgesic

For Adults and Children

No Artificial colors or Fragrances

2.0 OZ. (56.7 g)

1%FOR THE PLANET MEMBER